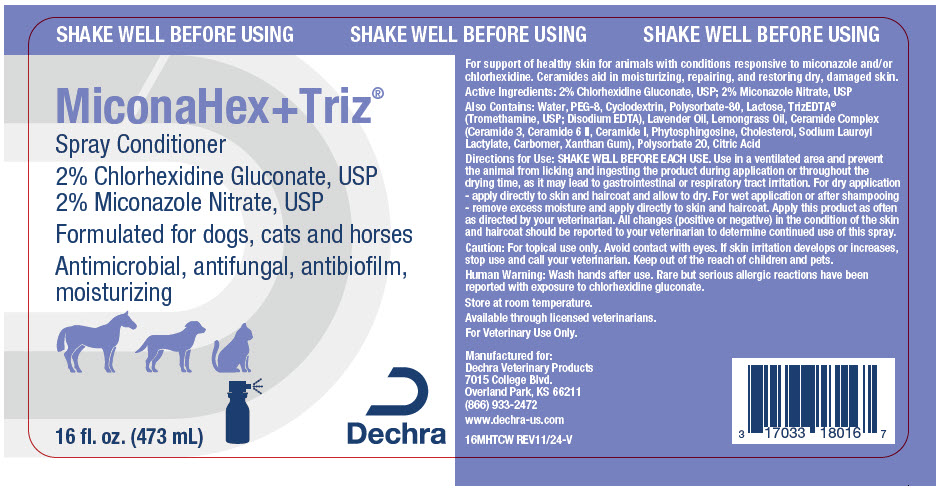 DRUG LABEL: MiconaHex plus Triz Conditioner
NDC: 17033-176 | Form: SPRAY, SUSPENSION
Manufacturer: Dechra Veterinary Products
Category: animal | Type: OTC ANIMAL DRUG LABEL
Date: 20241213

ACTIVE INGREDIENTS: CHLORHEXIDINE GLUCONATE 20 mg/1 mL; MICONAZOLE NITRATE 20 mg/1 mL

MiconaHex+Triz®
Spray Conditioner

VETERINARY INDICATIONS

For support of healthy skin for animals with conditions responsive to miconazole and/or chlorhexidine. Ceramides aid in moisturizing, repairing, and restoring dry, damaged skin.

Active Ingredients: 2% Chlorhexidine Gluconate, USP; 2% Miconazole Nitrate, USP

Also Contains: Water, PEG-8, Cyclodextrin, Polysorbate-80, Lactose, TrizEDTA® (Tromethamine, USP; Disodium EDTA), Lavender Oil, Lemongrass Oil, Ceramide Complex (Ceramide 3, Ceramide 6 II, Ceramide 1, Phytosphingosine, Cholesterol, Sodium Lauroyl Lactylate, Carbomer, Xanthan Gum), Polysorbate 20, Citric Acid

DOSAGE AND ADMINISTRATION

Directions for Use: SHAKE WELL BEFORE EACH USE. Use in a ventilated area and prevent the animal from licking and ingesting the product during application or throughout the drying time, as it may lead to gastrointestinal or respiratory tract irritation. For dry application - apply directly to skin and haircoat and allow to dry. For wet application or after shampooing - remove excess moisture and apply directly to skin and haircoat. Apply this product as often as directed by your veterinarian. All changes (positive or negative) in the condition of the skin and haircoat should be reported to your veterinarian to determine continued use of this spray.

SAFE HANDLING WARNING

Caution: For topical use only. Avoid contact with eyes. If skin irritation develops or increases, stop use and call your veterinarian. Keep out of the reach of children and pets.

WARNINGS

Human Warning: Wash hands after use. Rare but serious allergic reactions have been reported with exposure to chlorhexidine gluconate.

STORAGE AND HANDLING

Store at room temperature.

Available through licensed veterinarians.

For Veterinary Use Only.

Manufactured for:
Dechra Veterinary Products
7015 College Blvd.
Overland Park, KS 66211
(866) 933-2472
www.dechra-us.com

16MHTCW REV11/24-V

PRINCIPAL DISPLAY PANEL - 473 mL Bottle Label

SHAKE WELL BEFORE USING

MiconaHex+Triz®
Spray Conditioner

2% Chlorhexidine Gluconate, USP
2% Miconazole Nitrate, USP

Formulated for dogs, cats and horses
Antimicrobial, antifungal, antibiofilm,
moisturizing

16 fl. oz. (473 mL)

Dechra